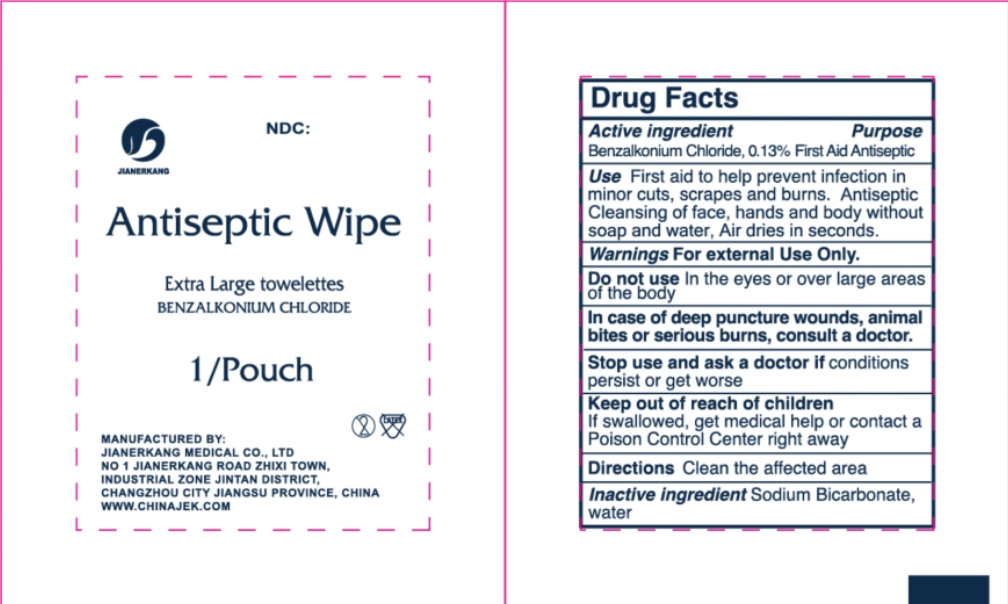 DRUG LABEL: Antiseptic Wipe
NDC: 34645-0024 | Form: CLOTH
Manufacturer: Jianerkang Medical Co., Ltd
Category: otc | Type: HUMAN OTC DRUG LABEL
Date: 20240606

ACTIVE INGREDIENTS: BENZALKONIUM CHLORIDE 1.3 mg/1 mL
INACTIVE INGREDIENTS: WATER; SODIUM BICARBONATE

Antiseptic Wipe

Active ingredient

Benzalkonium Chloride, 0.13%

Purpose

First Aid Antiseptic

Use

First aid antiseptic to help prevent infection in minor cuts, scrapes, and burns. Antiseptic Cleansing of face, hands and body without soap and water, Air dries in seconds.

Warnings

- For external use only.

Do not use

- in the eyes or over large areas of the body

Stop use and consult a doctor if

conditions persist or gets worse

Keep out of reach of children.

If swallowed, get medical help or contact a Poison Control Center right away

Directions

Clean the affected area

Inactive ingredients

Sodium Bicarbonate, water